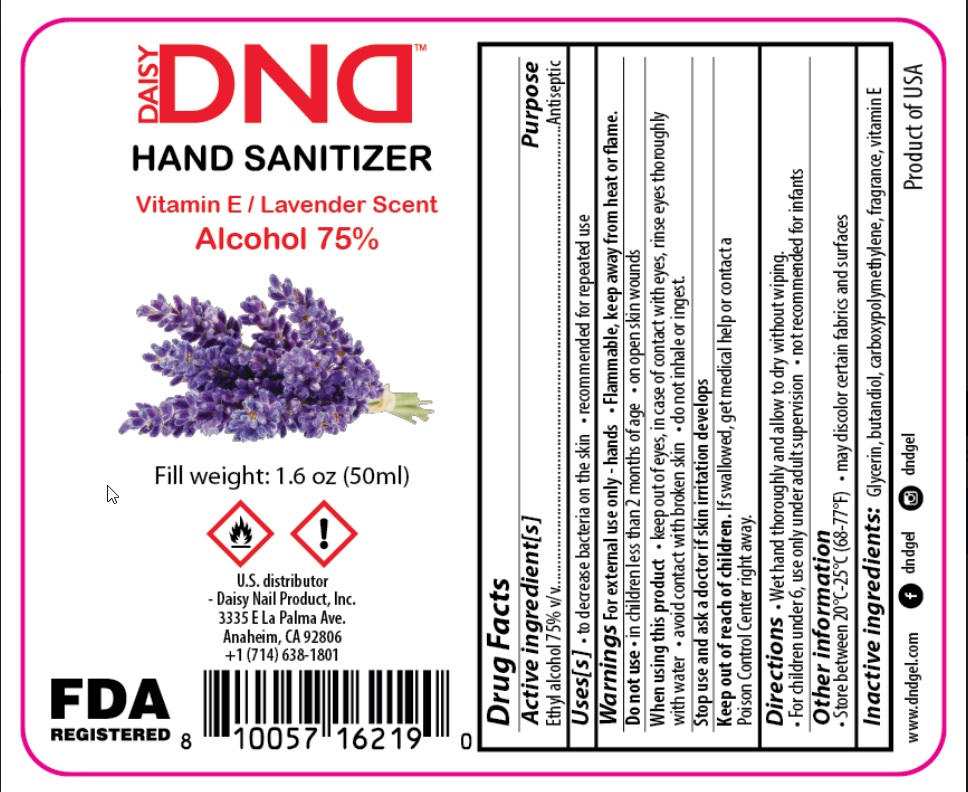 DRUG LABEL: Daisy DND Lavender scent hand sanitizer
NDC: 78951-006 | Form: GEL
Manufacturer: DAISY NAIL PRODUCTS, INC.
Category: otc | Type: HUMAN OTC DRUG LABEL
Date: 20201013

ACTIVE INGREDIENTS: ALCOHOL 75 mL/100 mL
INACTIVE INGREDIENTS: GLYCERIN; BUTANEDIOL (MIXED ISOMERS); CARBOMER HOMOPOLYMER, UNSPECIFIED TYPE; FRAGRANCE LAVENDER & CHIA F-153480

Active Ingredient

Ethyl Alcohol 75% v/v.

Purpose

Antiseptic

Use

- To decrease bacteria on the skin.
- Recommended for repeated use.

Warnings

For external use only. Flammable. Keep away from heat or flame

Do not use

- in children less than 2 months of age
- on open skin wounds

When using this product

- keep out of eyes. In case of contact with eyes, rinse eyes thoroughly with water.
- avoid contact with broken skin
- do not inhale or ingest.

Stop use and ask a doctor if skin irritation develops.

Keep out of reach of children. If swallowed, get medical help or contact a Poison Control Center right away.

Directions

- Wet hand thoroughly and allow to dry without wiping.
- For children under 6, use only under adult supervision.
- Not recommended for infants.

Other information

- Store between 20°C-25°C (68-77°F).
- May discolor certain fabrics and surfaces.

Inactive ingredients

Glycerin, butandiol, carboxypolymethylene, fragrance, vitamin E.